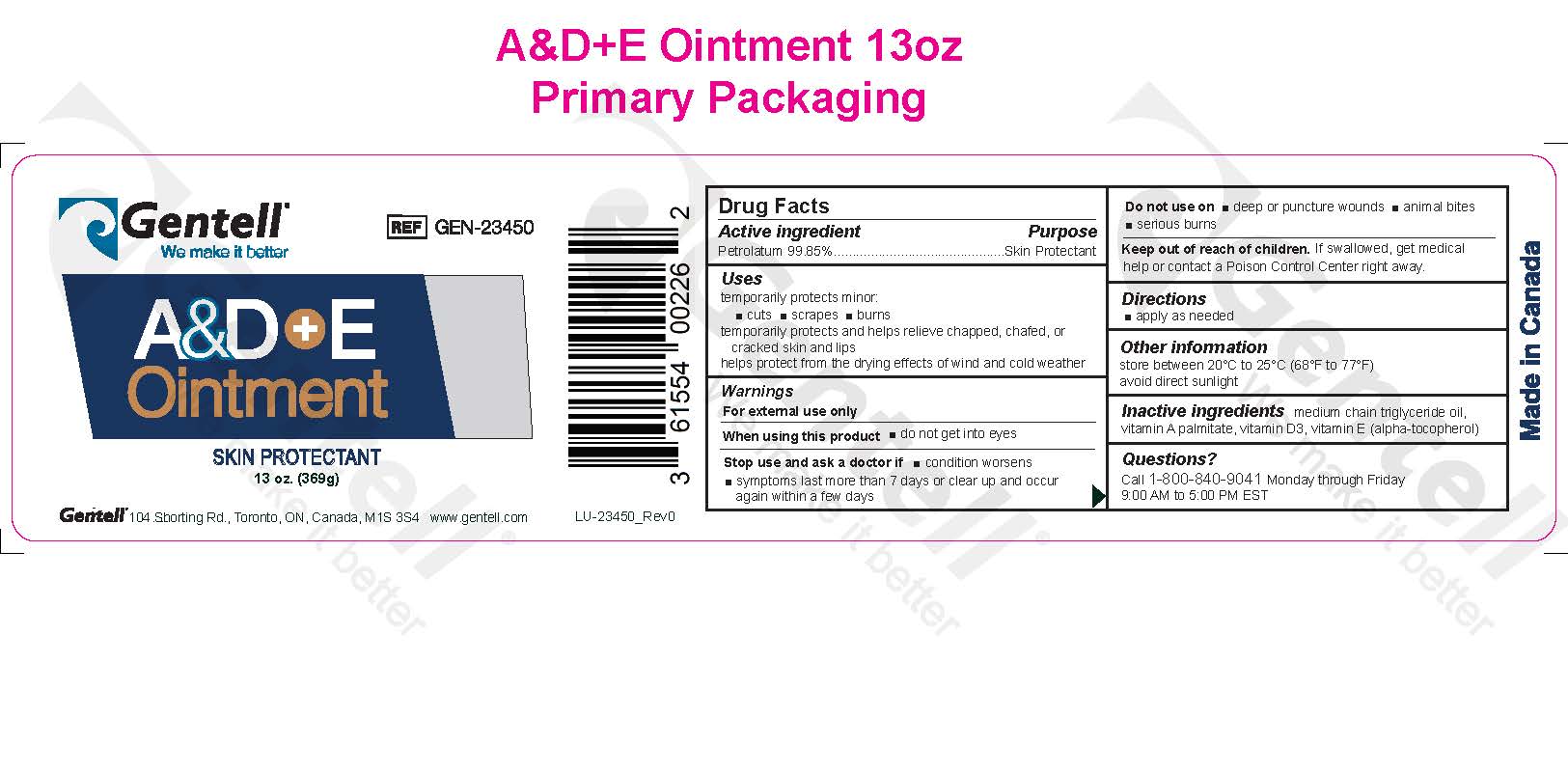 DRUG LABEL: A and D plus E
NDC: 64772-200 | Form: OINTMENT
Manufacturer: Derma Sciences Canada Inc.
Category: otc | Type: HUMAN OTC DRUG LABEL
Date: 20250722

ACTIVE INGREDIENTS: PETROLATUM 0.9985 g/1 g
INACTIVE INGREDIENTS: CHOLECALCIFEROL; VITAMIN A PALMITATE; .ALPHA.-TOCOPHEROL; MEDIUM-CHAIN TRIGLYCERIDES

ACTIVE INGREDIENT

Petrolatum 99.85%

PURPOSE

Skin Protectant

Uses

temporarily protects minor:

- cuts
- scrapes
- burns

temporarily protects and helps relieve chapped, chafed, or cracked skin and lips

helps protect from the drying effects of wind and cold weather

WARNINGS

For external use only

When using this product

- do not get into eyes

Stop use and ask a doctor if

- conditions worsens
- symptoms last moe than 7 days or clear ip and occur again within a few days

Do not use on

- deep puncture wounds
- animal bites
- serious burns

Keep out of reach of children. if sallowed , get medical help or contact a Poison Control center right away.

When using this product

- do not get into eyes

Stop use and ask a doctor if

- condition worsens
- symptoms last more than 7 days or clear up and occur again within a few days

Stop use and ask a doctor if

- condition worsens
- symptoms last more than 7 days or clear up and occur again within a few days

Do not use on

- deep or puncture wounds
- animal bites
- serious burns

Keep out of reach of children.

OTHER SAFETY INFORMATION

For external use only

If swallowed, get medical help or contact a Poison Control Center right away.

Directions

- apply as needed

DOSAGE AND ADMINISTRATION

apply as neede

Other information

store between 20°C to 25°C (68°F to 77°F)

avoid direct sunlight

Inactive ingredients

medium chain triglyceride oil, vitamin A palmitate, vitamin D3, vitamin E (alpha-tocopherol)

Questions?

Call 1-800-840-9041 Monday through Friday 9:00 AM to 5:00 PM EST

PACKAGE LABEL

Gentell We make it better

GEN-23450

A&D+E ointment

Skin Protectant

13 oz. (369 g)

Gentell 104 Shorting Rd, Toronto , ON, Canada M1S 3S4 www.gentell.com